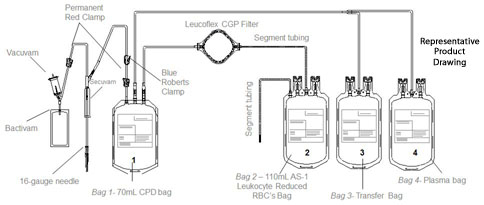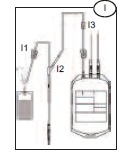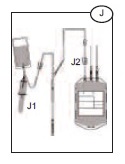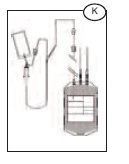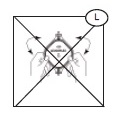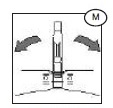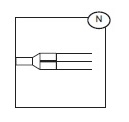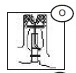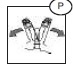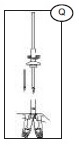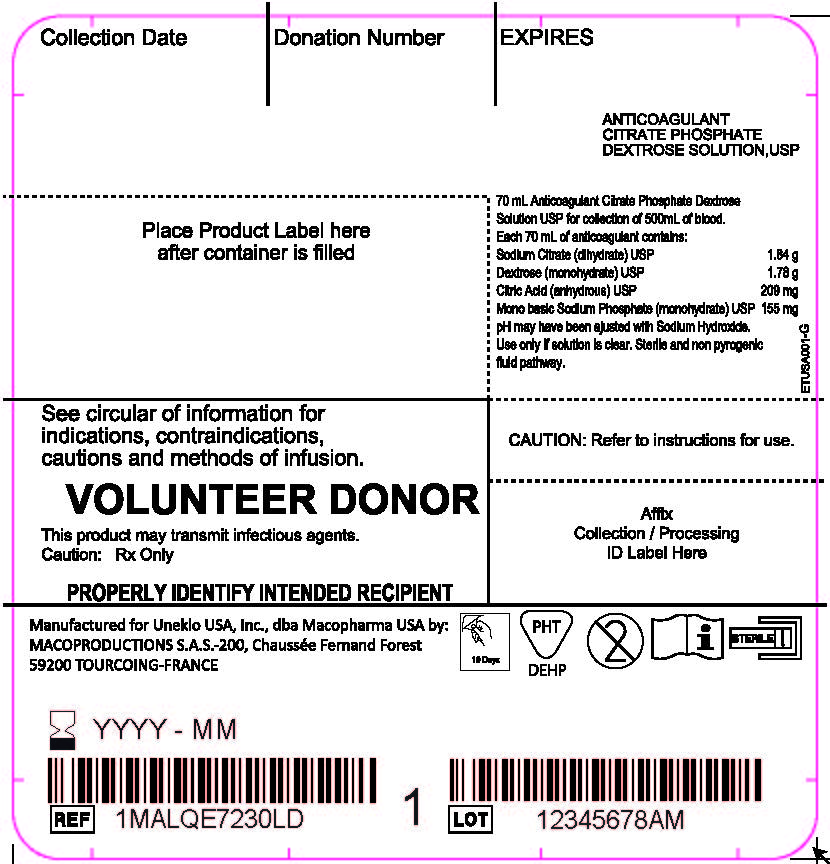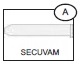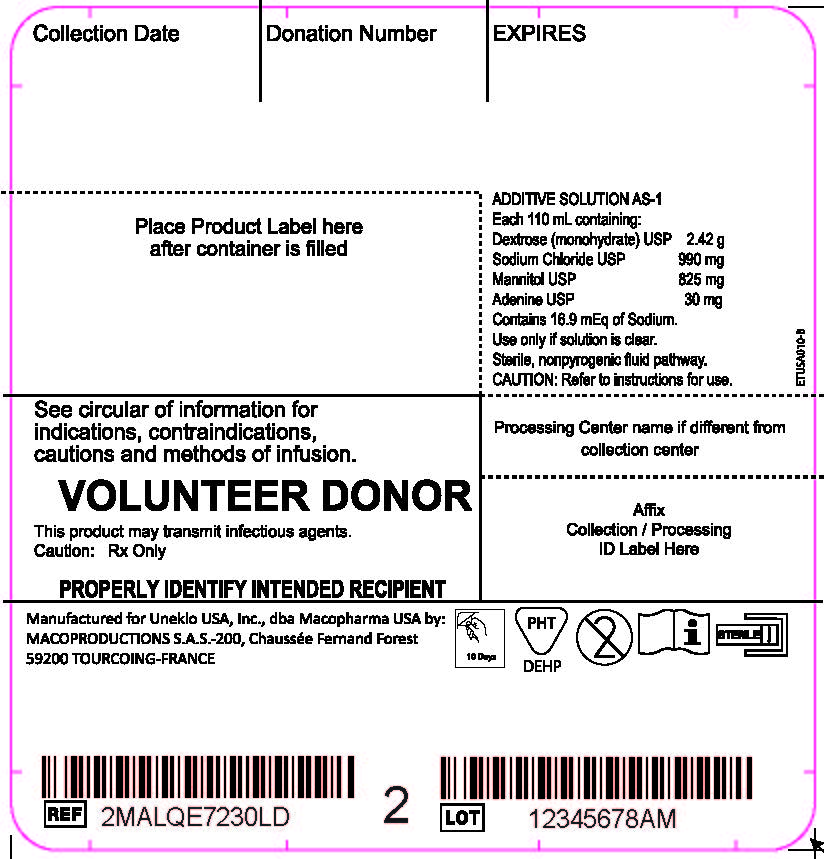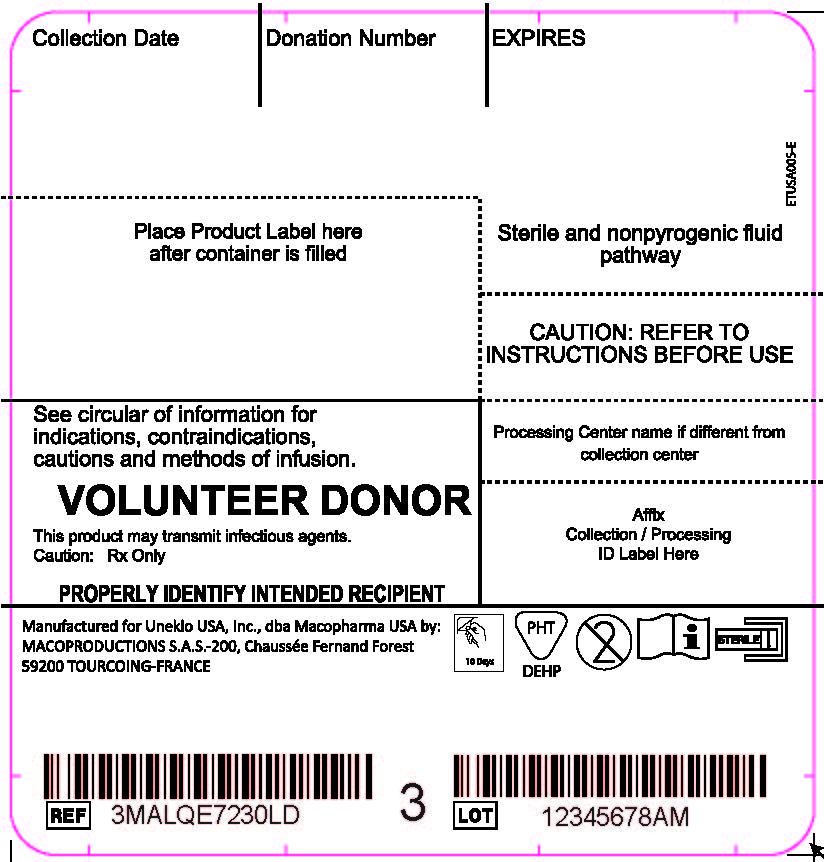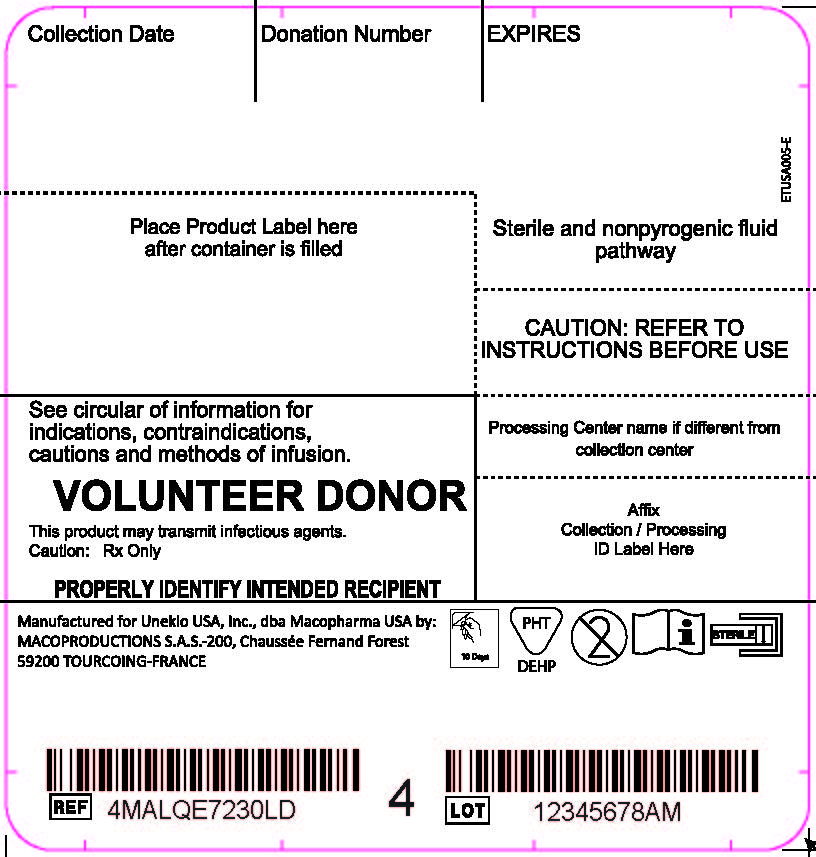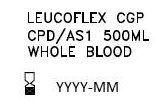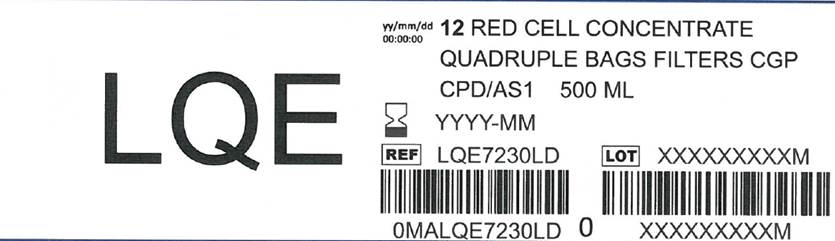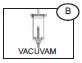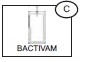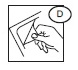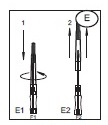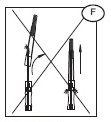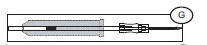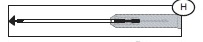 DRUG LABEL: Leucoflex CGP
NDC: 14498-002 | Form: KIT | Route: INTRAVENOUS
Manufacturer: Maco Productions
Category: prescription | Type: HUMAN PRESCRIPTION DRUG LABEL
Date: 20251223

ACTIVE INGREDIENTS: SODIUM CITRATE 1.84 g/70 mL; DEXTROSE MONOHYDRATE 1.78 g/70 mL; ANHYDROUS CITRIC ACID 209 mg/70 mL; SODIUM PHOSPHATE, MONOBASIC, MONOHYDRATE 155 mg/70 mL; DEXTROSE MONOHYDRATE 2.42 g/110 mL; SODIUM CHLORIDE 990 mg/110 mL; MANNITOL 825 mg/110 mL; ADENINE 30 mg/110 mL

Anticoagulant Citrate Phosphate Dextrose Solution USP (CPD)
With an Integral Container of Additive Solution (AS-1) Preservative,
And an Integral Leucoflex CGP Leukocyte Reduction Filter for Red Blood Cells

Description

The Leucoflex CGP product consists of a blood collection system with 70ml of CPD for the collection of 500±50ml of blood and 100ml of AS-1 Additive Solution. They are supplied with sterile, non-pyrogenic fluid pathways. The product as supplied includes an in-line leukocyte reduction filter known as Leucoflex CGP, storage containers for blood components and tubing, a sample diversion pouch (Bactivam), a vacuum tube adapter (Vacuvam), and a protective shield for the used needle (Secuvam).

Representative Product Drawing

Intended Use

The "Leucoflex CGP Leukocyte Reduction Filter" is intended for the leukocyte reduction of Red Blood Cells prepared from whole blood stored at 1-6°C up to 24 hours after collection. The collection set provides for subsequent preparation of AS-1 Red Blood Cells, leukocytes Reduced (adenine saline added) and plasma in a closed system.

The AS-1 Red Blood Cells, leukocytes Reduced and plasma may then be stored for the maximum allowable dating periods.

WARNING

- Avoid contact with sharp objects.
- DO NOT USE if the overwrap or blood bag system shows any signs of deterioration.
- DO NOT USE if the solutions are not clear.
- Dispose of all system components that have been contaminated with blood in a biohazard container as per your institution's SOP.
- Dispose of all sharps as per your institution's SOP.

CAUTIONS

- Do not fold or squeeze the Leucoflex CGP filter. Inappropriate handling may adversely affect filtration.
- Check for kinks in the tubing prior to collection and filtration.
- Rx only.

The protective shield for needle Secuvam (A) and the vacuum tube adapter Vacuvam (B) features of the collection set aid in the safe collection of vacuum tube samples from the sample diversion pouch Bactivam (C) and the disposal of donor needles after blood collectin by providing protection from accidental needlestick.

All or part of this medical device is made of PVC plasticized with DEHP. According to some studies, DEHP could potentially be harmful to the reproductive system of male fetuses. The prescriber is solely responsible for choosing to use this device on women who are either pregnant or breast-feeding, or on young male infants. Nevertheless, DEHP-plasticized PVC is in compliance with the European Pharmacopeia.

All manufacturing processes and all components in contact with the donors, the users and the blood components dedicated to the patients are not made with natural rubber latex.

COLLECTION AND SAMPLING PROCEDURE

INSTRUCTION FOR USE

Before Donation

1) Peel open the transparent overwrap (D) using the corner flap.

2) Support blood bag system as far as possible below donor arm, ideally on an automated blood mixer.

Note: it is recommended that the primary bag on the mixer lies with the tubing on the lower side of the mixer holding plate.

3) Apply tourniquet or pressure cuff (inflate to approximately 60 mm Hg).

4) Prepare venipuncture site as per your SOP.

5) Ensure that the donor line is not twisted or tangled.

Venipuncture

1) Open the needle cap (E1) using the following procedure:

a) Twist the needle cap, thus breaking the seal.

b) Lift the cap off of the needle (E2) in a straight line taking special care not to touch the needle in the process (F). Keep hands behind the needle at all times during set use and disposal.

2) Perform the venipuncture.

3) After the needle has been inserted, introduce the Secuvam onto the hub of the needle.

4) Tape the Secuvam onto the donor's arm.

Note: if the Secuvam causes discomfort to the donor or decreases the blood flow because of the angle of the needle, leave the Secuvam on the tubing, behind the needle hub (G) during collection. Secure the needle into the Secuvam at the end of the donation (H).

After Venipuncture

1) Ensure that the clamp between the Bactivam pouch and the donation line is open.

2) Ensure that the Bactivam pouch is held below the level of the venipuncture site, and is supported at all times.

3) Allow blood to run into the Bactivam pouch until the pouch fills (approximately 30ml) (I).

4) Close the red clamp (I1) on the transfer line to the Bactivam pouch, by holding the clamp in one hand and squeezing the two edges together, until it locks (a click may be heard).

Note: the red clamp cannot be opened after it has snapped shut.

5) Break the break-away cannula (I2) on the donor line by holding the cannula in one hand and the plastic Y-junction in the other and snapping the cannula both left and right to ensure a clean break. Allow the donation procedure to continue, ensuring that the blood bag is mixed immediately when blood flows into the primary bag.

Note: This step may be done prior to venipuncture if the Blue Roberts clamp (I3) on the donor line is closed prior to breaking the break-away cannula.

6) If using an automated mixer, open the mixer clamp and start the mixer at this point.

Note: it is recommended that the primary bag on the mixer lies with the tubing on the lower side of the mixer holding plate.

7) After approximately 50 ml of blood enters the primary bag, mix thoroughly (when possible).

Note: Collect the quantity of blood stated on the blood bag label.

Sampling Procedure

Note: this is done during the donation. Avoid air in the collection of sample tubes from the diversion pouch to ensure adequate sample volume and avoid hemolysis.

1) Hold the Bactivam pouch with the Vacuvam below it (J), to ensure good blood flow from the pouch to the sampling device, and no introduction of air into the sampling tubes.

2) Remove the cap of the Vacuvam sampling device, and retain for later use (when possible).

3) Introduce a vacuum sampling tube by holding the barrel of the Vacuvam and directing the sample tube cap directly onto the needle inside the device (J1).

4) Blood is drawn automatically into the sampling tube, stopping at the appropriate volume.

5) When the sample tube stops filling, withdraw the tube, ensuring that the tube is pulled out of the barrel in a straight line.

6) Repeat the sampling procedure steps (3 to 5) with all remaining sampling tubes.

7) When all samples have been taken, replace the Vacuvam cap to prevent accidental access to the interior needle (when possible).

8) Mix the blood in the primary bag regularly (approximately every 100 ml or every minute).

After Donation

1) Once the required volume of blood has been collected, close the red clamp on the donor line (J2), at least 12 inches above the primary bag.

Note: if necessary, place a Hemostat on the colletion line just below the Secuvam.

2) Release the pressure cuff or tourniquet, and immediately mix the whole blood in the primary bag.

Note: if the needle was taped to the arm, and not the Secuvam, remove the tape from the needle before pulling the needle into the Secuvam (disregard step 3).

3) Remove the tape holding the Secuvam in place.

4) Remove the needle by gently pulling the needle into the barrel of the Secuvam while supporting the Secuvam with one hand (a click may be heard).

Note: if necessary, step 4 may be done before step 3.

5) Remove and discard the cap (if relevant) from the barrel of the Vacuvam, into an appropriate container.

6) Insert the Secuvam needle protector into the barrel of the Vacuvam sampling device.

7) After removing the blood from the mixer/trip scale, mix the blood unit thoroughly.

8) If the donor line is to be used for quality control, strip the line as per procedure (at least 3 times), heat-seal (place clips) and cut (between the clips), leaving sufficient line for testing purposes.

Note: if it is necessary to strip the donor line, it is recommended to strip within 4 minutes of the end of the donation, in order to avoid introducing clots into the blood bag.

9) Ideally, heat-seal the donor line as close as possible to the pack (~1 inch). Alternatively, place clips close to the blood pack and cut between the clips. Mix thoroughly during and immediately after the procedure.

Note: this is an in-line filter system; there is no need to keep the donor line for cross-matching segments.

10) Remove and discard the donor line (K) with the two red clamps, Blue Roberts clamp, Bactivam, Vacuvam and Secuvam as per SOP.

Note: the completely protected needle after securing the Secuvam inside the rigid Vacuvam sleeve can be disposed of in general biowaste vs. a sharps container.

Opening needle cap

COMPONENT PREPARATION GENERAL

CAUTION:
Do not fold or manhandle the filters (L).
Do not apply pressure, either mechanical or human, to increase the flow rate of the filter.

- Units with decreased or extended filtration times may not be adequately leukoreduced, and should be evaluated for residual leukocytes and red blood cell recovery before release. Consult training materials for more information on expected length of filtration times and the applicable hold periods in clinical study data.

- Failure to achieve and maintain a closed system throughout processing results in a product that must be stored at 1 to 6 C and transfused within 24 hours.

- The AS-1 additive solution must be added to the red blood cells without delay after the separation of the plasma. Whole blood in CPD alone may be stored at 1 to 6 C for up to 21 days.

- The filter has been designed and validated to meet the criteria of a leukocytes reduction filter for Red Blood Cells. The filter's performance must be validated using your facility's standard operating procedure (SOP) on component preparation and handling. Any filtration that fails to meet the filtration specifications established by the facility's validation should be evaluated for residual leukocytes and red blood cell (RBC) recovery after filtration.

Note that unusual attributes such as sickle cell trait, cold agglutinins, blood clotting and gel formation, and poor mixing during collection and processing of components can contribute to the failure of a filtration to meet filtration specifications. Failure to adequately mix RBC with Additive Solution thoroughly prior to filtration can result in blocked filters.

BLOOD COMPONENTS SEPARATION

1) Obtain collected Whole Blood from 1-6 C storage container.

2) Mix the Whole Blood thoroughly.

3) Pack the collection system into a centrifuge as per your facility's standard operating procedure (SOP).

4) Centrifuge the blood, satellite bag, and additive solution bag together under conditions designed to produce a separation of plasma and red blood cells.

5) Place the centrifuged blood carefully into an extractor, and gently release the pressure plate.

6) Break the break-away cannula (M) on the tubing leading to the plasma bag by bending the cannula with a side-to-side motion.

7) Express Plasma into appropriate container.

8) If preparing Cryoprecipitate AHF (Anti-Hemophilic Factor) from this Plasma, place a temporary clamp between the 'Y' connector (N) and the bag for the final storage of plasma otherwise, add a permanent clamp.

9) If required, express the air from the plasma back into the RBC bag.

10) Heat seal and disconnect the Plasma bag. (If Cryoprecipitate is manufactured heat seal the tubing 1 inch before the Y connector).

Breaking the cannula

RED BLOOD CELLS LEUKOCYTES REDUCTION

1) Lift the additive solution (AS-1) bag above the RBC bag on the filtration rack or drip stand.

2) Break the break-away cannula on the RBC bag by bending the cannula with side-to-side motion.

3) Allow the additive solution to drain completely through the Leucoflex CGP filter into the RBCs without delay.

Note: Some additive solution will be left in the filter. DO NOT squeeze the filter in order to maximize the additive transfer to the RBCs.

4) Place a Hemostat on the tubing between the filter and the AS-1 RBCs bag.

5) Thoroughly, mix the AS-1 with the Red Blood Cells.

6) Hang the AS-1 RBCs bag on a filtration rack so that the outlet tubing of the Leucoflex CGP filter and the Leukocyte Reduced (LR) AS-1 RBC bag inlet tubing is fully extended and the LR AS-1 RBCs bag is freely hanging.

7) Remove the Hemostat and allow the blood to flow by gravity through the Leucoflex CGP filter into the LR AS-1 RBCs bag.

Note: Determine the status of the filtration as follows: if there is no blood flowing from below the filter, the filter is flat and the filter media is visible on the inlet side, filtration is complete.

8) Heat seal the segment tubing 1 inch below the Leucoflex CGP filter, and all along the segment tubing between the printed numbers.

9) Disconnect and discard the empty transfer bag, Leucoflex CGP filter, and tubing as per SOP.

10) Store the LR AS-1 Red Blood Cells, at 1-6 C for up to 42 days.

WARNING: if unit is spiked for any reason, storage is limited to 24 hours at 1 to 6 C before transfusion.

NOTE: If either face of the filter remains white, the Red Cell Concentrate has not been leucoreduced and must be discarded.

HANDLING OF PORT PROTECTORS

1) Using both hands tear the port protector as indicated. (O)

2) Hold down the port protector pieces with one hand. (P)

3) Using the free hand, take the spike and engage intor the port. (Q)

4) Twist the spike to secure fully in port. (Q)

LABELS

Bag 1 Anticoagulant Citrate Phosphate Dextrose Solution, USP; Bag 2 Additive Solution AS-1; Bag 3 Transfer Bag; Bag 4 Plasma Bag; Overwrap; Carton

Anticoagulant Citrate Phosphate Dextrose Solution, USP - Bag 1 Label

Additive Solution AS-1 - Bag 2 Label

TRANSFER BAG LABEL

PLASMA BAG LABEL

OVERWRAP LABEL

CARTON LABEL